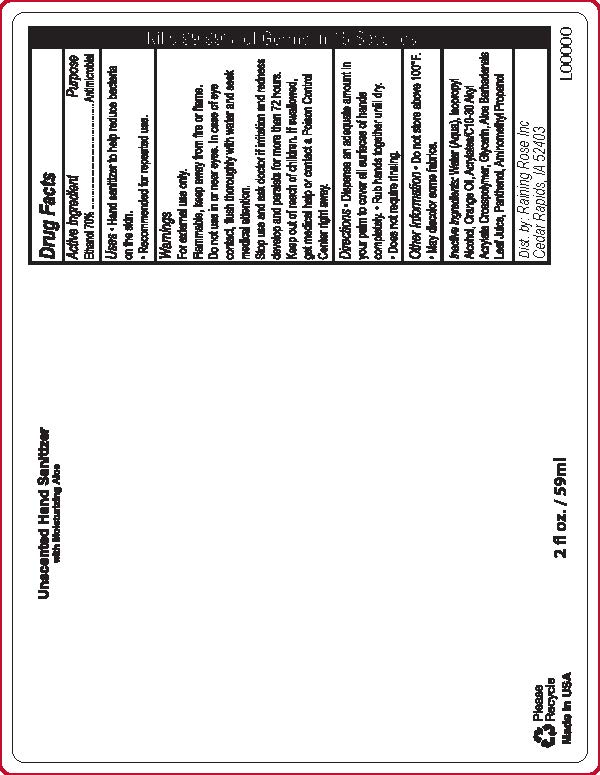 DRUG LABEL: Hand Sanitizer
NDC: 65692-2072 | Form: GEL
Manufacturer: Raining Rose, Inc
Category: otc | Type: HUMAN OTC DRUG LABEL
Date: 20210518

ACTIVE INGREDIENTS: ALCOHOL 70 mL/100 mL
INACTIVE INGREDIENTS: ORANGE OIL; CARBOMER INTERPOLYMER TYPE A (ALLYL SUCROSE CROSSLINKED); WATER; ISOPROPYL ALCOHOL; ALOE VERA LEAF; PANTHENOL; AMINOMETHYLPROPANOL; GLYCERIN

ACTIVE INGREDIENT

Ethanol 70%

PURPOSE

Antimicrobial

INDICATIONS AND USAGE

Hand Sanitizer to help reduce bacteria on the skin. Recommended for repeated use.

Warnings• For external use only
• Flammable, keep away from fire or flame
• Do not use in eyes. In case of eye contact flush
thoroughly with water and seek medical attention.

• Stop use and ask doctor if irritation and redness develop and persists for more than 72 hours.

• Keep out of reach of children. If swallowed, get medical help or contact a Poison Control Center right away.

Keep Out of Reach of Children. If swallowed, get medical help or contact a Poison Control Center right away.

Directions
• Dispense an adequate amount in your palm to cover all surfaces of hands completely.

• Rub hands together until dry. • Does not require rinsing.

Other Information
• Do not store above 105°F.
• May discolor some fabrics.

INACTIVE INGREDIENT

Inactive Ingredients: Water (Aqua), Isopropyl Alcohol, Orange Oil, Acrylates/C10-30 Akyl Acrylate Crosspolymer, Glycerin, Aloe Barbadensis Leaf Juice, Panthenol, Aminomethyl Propanol.